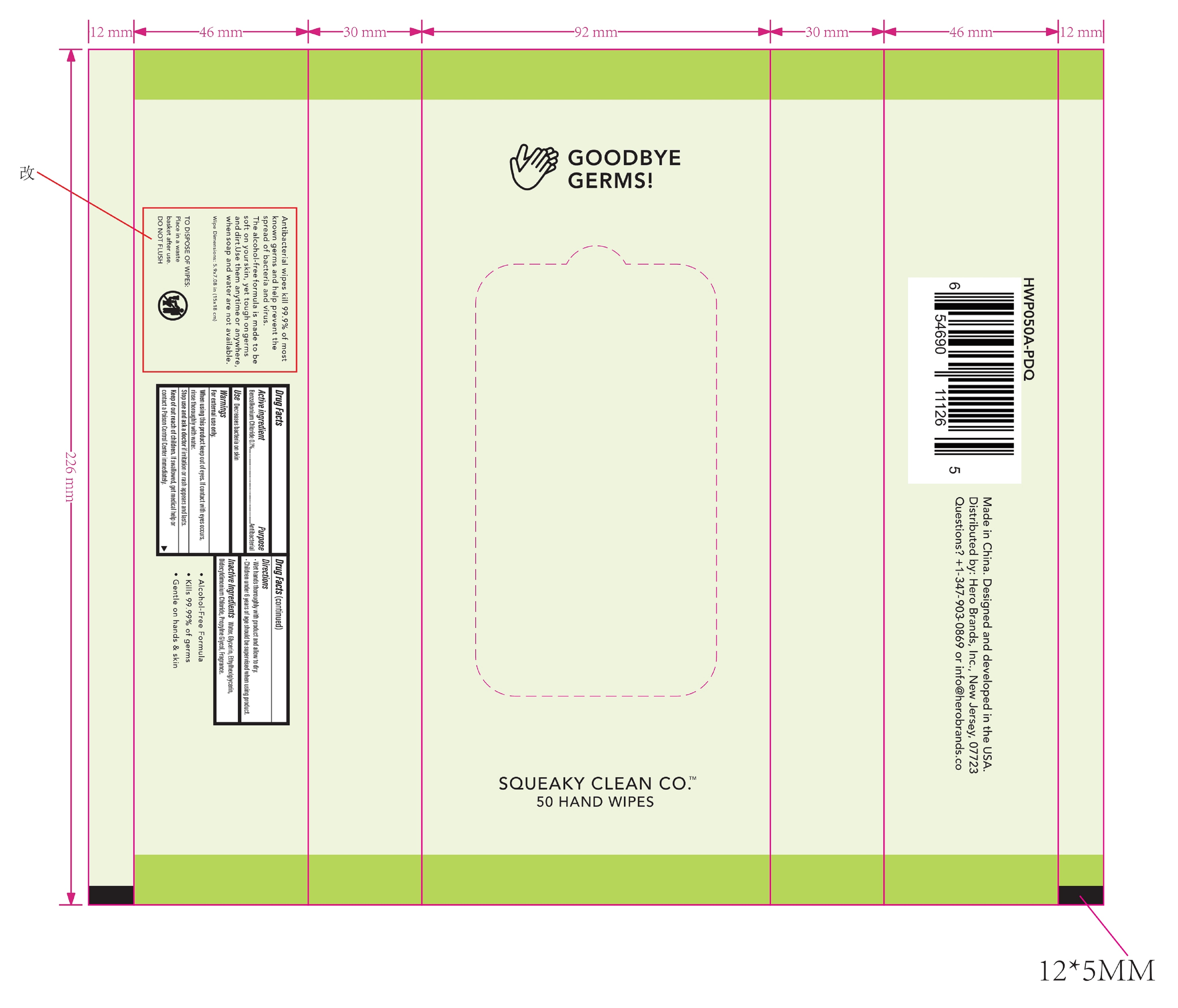 DRUG LABEL: 50 Pack Antibacterial Hand Wipes - Aloe
NDC: 90114-303 | Form: CLOTH
Manufacturer: Hero Brands, Inc.
Category: otc | Type: HUMAN OTC DRUG LABEL
Date: 20200826

ACTIVE INGREDIENTS: BENZALKONIUM CHLORIDE 0.01 g/100 1
INACTIVE INGREDIENTS: ALOE; WATER; ETHYLHEXYLGLYCERIN; DIDECYLDIMONIUM CHLORIDE; GLYCERIN; PROPYLENE GLYCOL

90114-303 50 Pack Antibacterial Hand Wipes - Aloe

Active Ingredient(s)

Benzalkonium Chloride 0.1% , Antibacterial

Purpose

Antibacterial, Hand wipes

Use

Decreases bacteria on skin.

Warnings

For external use only. Keep away from fire or flame

Do not use

- in children less than 2 months of age
- on open skin wounds

When using this product keep out of eyes, If contact with eyes occurs, rinse thoroughly with water.

Stop use and ask a doctor if irritation or rash appears and lasts.

Keep out of reach of children. If swallowed, get medical help or contact a Poison Control Center immediately.

Directions

- Wet hands thoroughly with product and allow to dry.
- Children under 6 years of age should be supervised when using product.

Inactive ingredients

Water, Glycerin, Ethylhexlglycerin, Didecyldimonium Chloride, Propylne Glycol, Fragrance.

Package Label - Principal Display Panel

50 HAND WIPES NDC: 90114-303-01